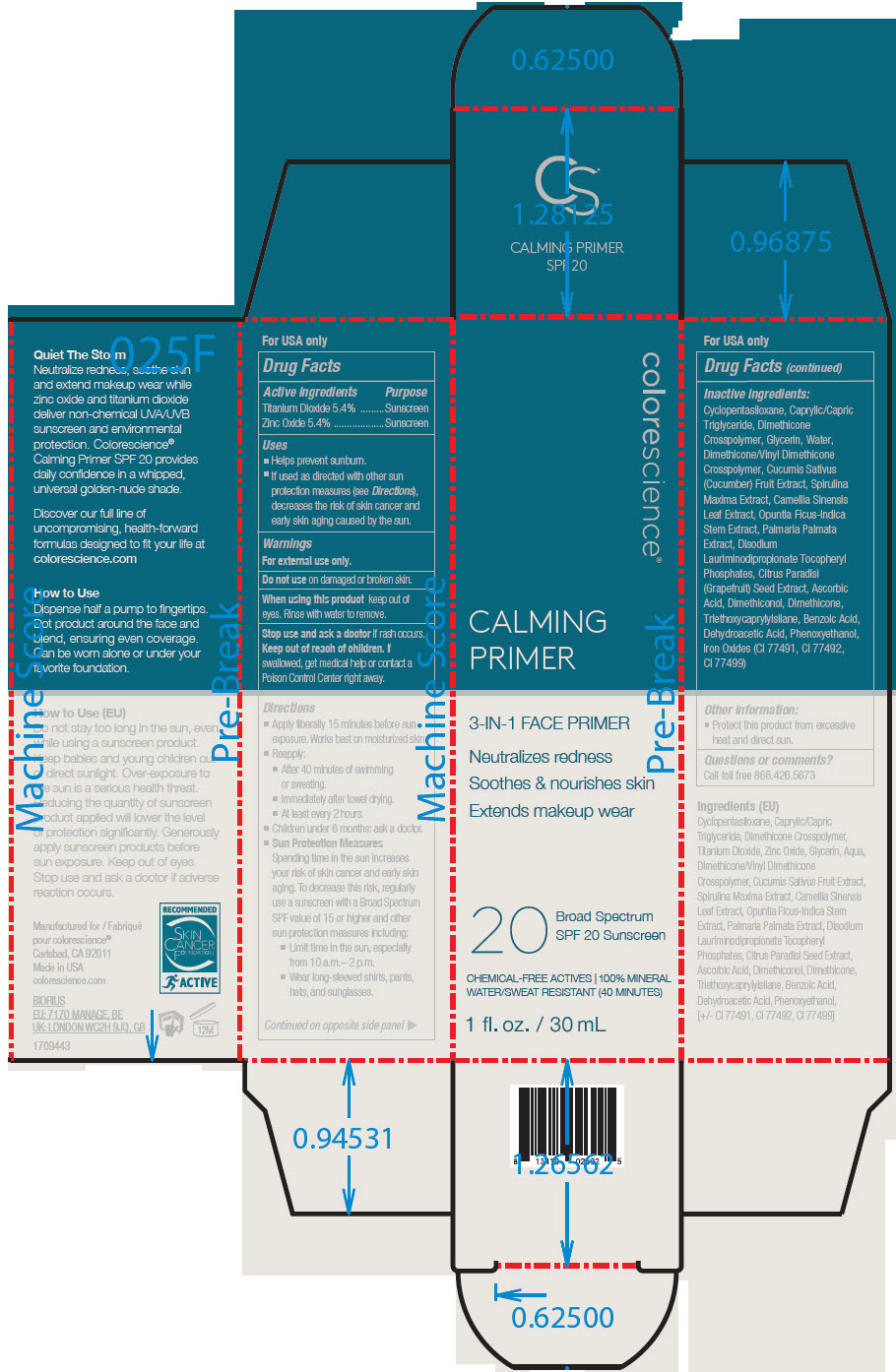 DRUG LABEL: Calming Primer SPF 20
NDC: 68078-040 | Form: LIQUID
Manufacturer: Colorescience
Category: otc | Type: HUMAN OTC DRUG LABEL
Date: 20241213

ACTIVE INGREDIENTS: Titanium Dioxide 54 mg/1 mL; Zinc Oxide 54 mg/1 mL
INACTIVE INGREDIENTS: Cyclomethicone 5; Dimethicone Crosspolymer (450000 MPA.S AT 12% IN Cyclopentasiloxane); MEDIUM-CHAIN TRIGLYCERIDES; Water; Glycerin; Dimethicone; Disodium Lauriminodipropionate Tocopheryl Phosphates; Dimethiconol (100000 CST); ARTHROSPIRA MAXIMA; FERRIC OXIDE YELLOW; Citrus Paradisi Seed; Phenoxyethanol; Triethoxycaprylylsilane; Ascorbic Acid; Green Tea Leaf; PALMARIA PALMATA; FERRIC OXIDE RED; Opuntia Ficus-Indica Stem; FERROSOFERRIC OXIDE; Benzoic Acid; Dehydroacetic Acid

Calming Primer SPF 20

Drug Facts

ACTIVE INGREDIENT

Active ingredients | Purpose
Titanium Dioxide 5.4% | Sunscreen
Zinc Oxide 5.4% | Sunscreen

Uses

- Helps prevent sunburn.
- If used as directed with other sun protection measures (see Directions), decreases the risk of skin cancer and early skin aging caused by the sun.

Warnings

For external use only.

Do not use on damaged or broken skin.

When using this product keep out of eyes. Rinse with water to remove.

Stop use and ask a doctor if rash occurs.

Keep out of reach of children. If swallowed, get medical help or contact a Poison Control Center right away.

Directions

- Apply liberally 15 minutes before sun exposure. Works best on moisturized skin.
- Reapply:
  - After 40 minutes of swimming or sweating.
  - Immediately after towel drying.
  - At least every 2 hours.
- Children under 6 months: ask a doctor.
- Sun Protection Measures
  Spending time in the sun increases your risk of skin cancer and early skin aging. To decrease this risk, regularly use a sunscreen with a Broad Spectrum SPF value of 15 or higher and other sun protection measures including:
  - Limit time in the sun, especially from 10 a.m.– 2 p.m.
  - Wear long-sleeved shirts, pants, hats, and sunglasses.

Inactive ingredients

Cyclopentasiloxane, Caprylic/Capric Triglyceride, Dimethicone Crosspolymer, Glycerin, Water, Dimethicone/Vinyl Dimethicone Crosspolymer, Cucumis Sativus (Cucumber) Fruit Extract, Spirulina Maxima Extract, Camellia Sinensis Leaf Extract, Opuntia Ficus-Indica Stem Extract, Palmaria Palmata Extract, Disodium Lauriminodipropionate Tocopheryl Phosphates, Citrus Paradisi (Grapefruit) Seed Extract, Ascorbic Acid, Dimethiconol, Dimethicone, Triethoxycaprylylsilane, Benzoic Acid, Dehydroacetic Acid, Phenoxyethanol, Iron Oxides (CI 77491, CI 77492, CI 77499)

Other information

- Protect this product from excessive heat and direct sun.

Questions or comments?

Call toll free 866.426.5673

PRINCIPAL DISPLAY PANEL - 30 mL Bottle Carton

colorescience®

CALMING
PRIMER

3-IN-1 FACE PRIMER

Neutralizes redness

Soothes & nourishes skin

Extends makeup wear

20
Broad Spectrum
SPF 20 Sunscreen

CHEMICAL-FREE ACTIVES | 100% MINERAL
WATER/SWEAT RESISTANT (40 MINUTES)

1 fl. oz. / 30 mL